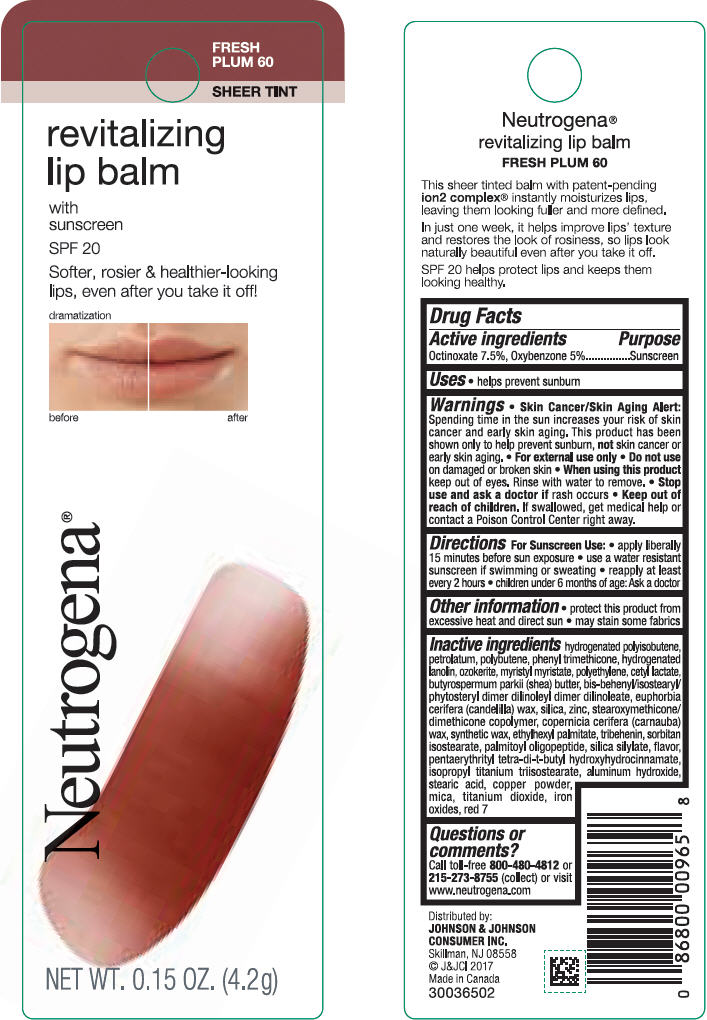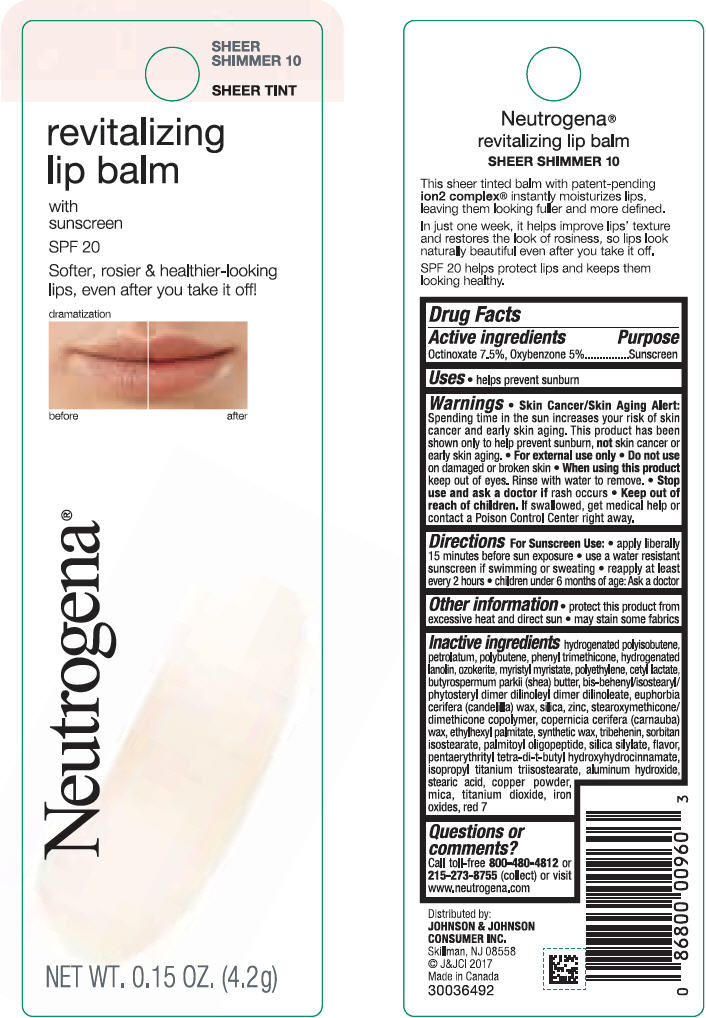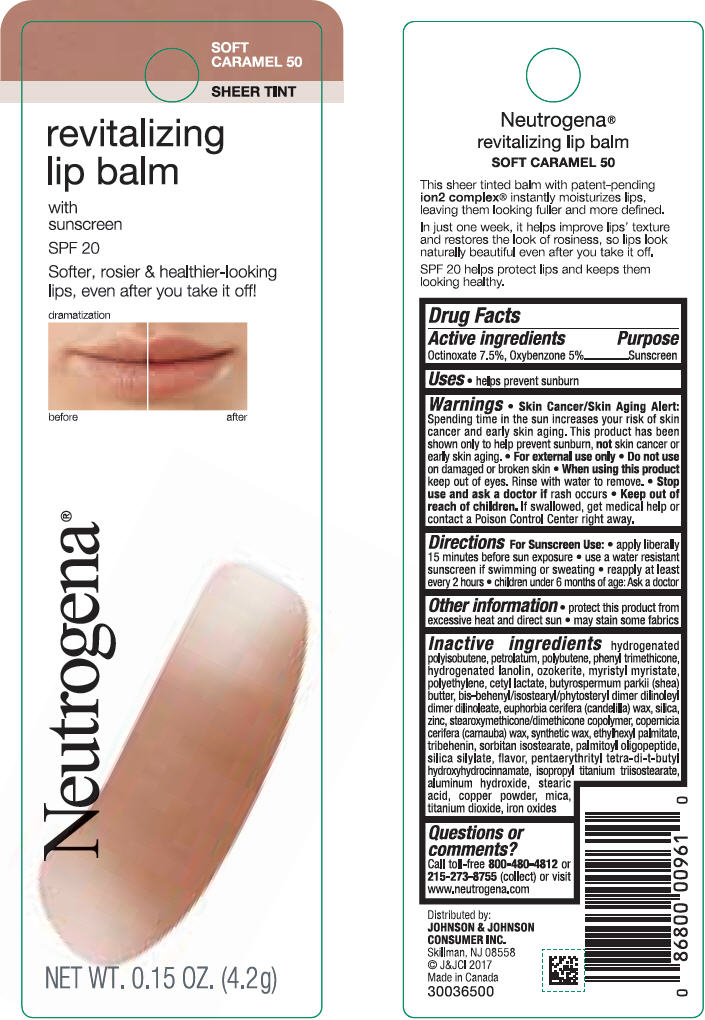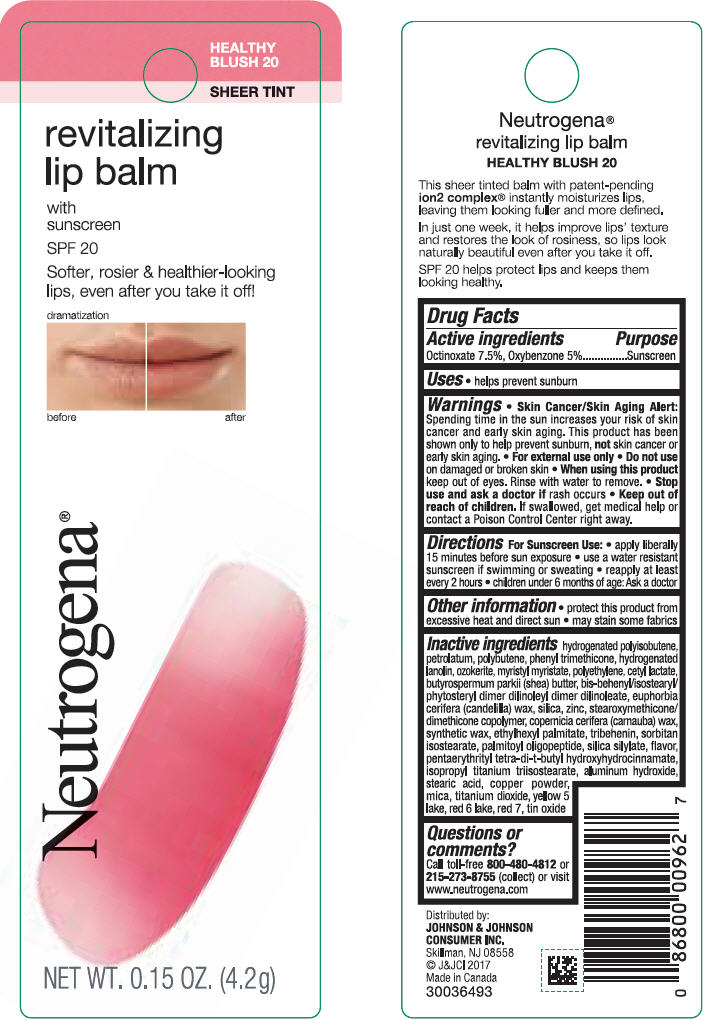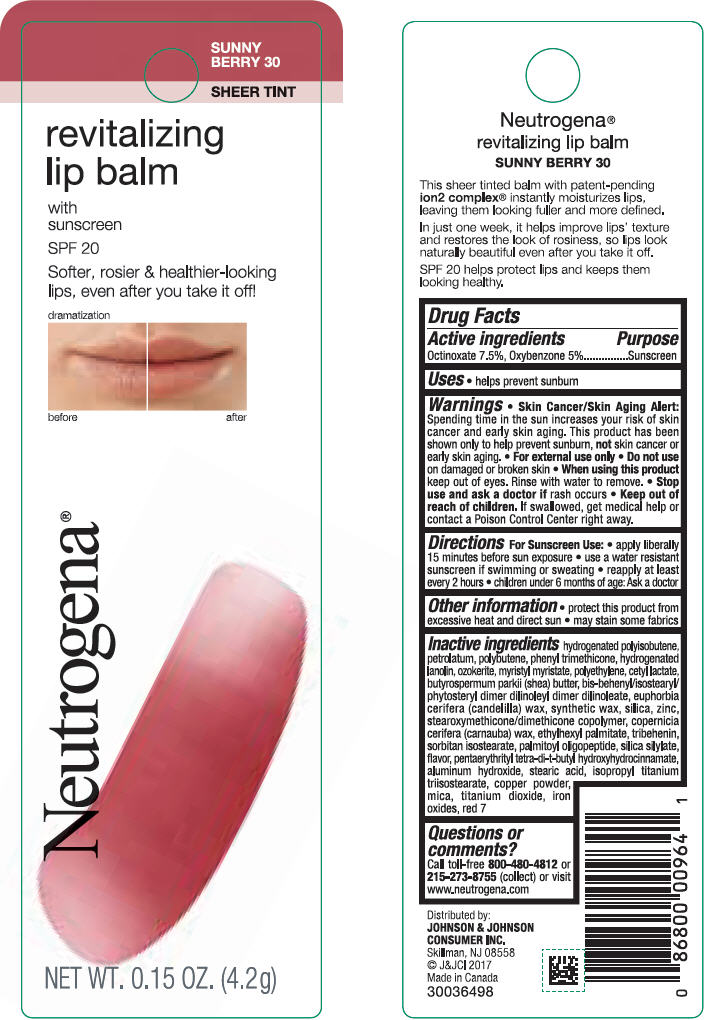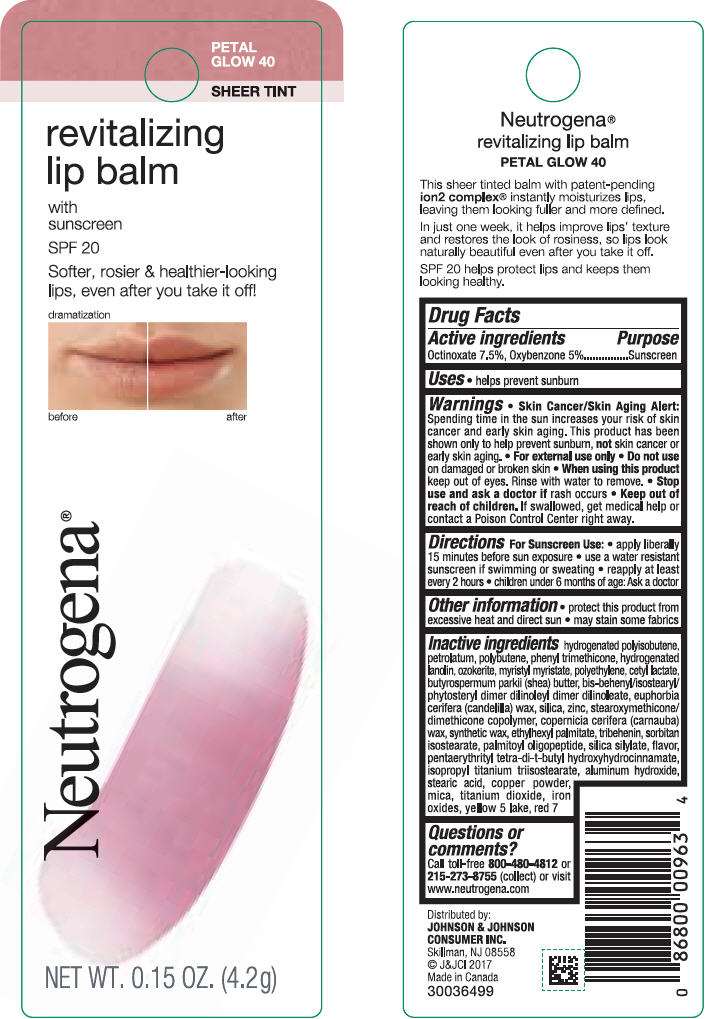 DRUG LABEL: Neutrogena Revitalizing Lip Balm
NDC: 69968-0256 | Form: LIPSTICK
Manufacturer: Kenvue Brands LLC
Category: otc | Type: HUMAN OTC DRUG LABEL
Date: 20241111

ACTIVE INGREDIENTS: OCTINOXATE 75 mg/1 g; OXYBENZONE 50 mg/1 g
INACTIVE INGREDIENTS: HYDROGENATED POLYBUTENE (1300 MW); PETROLATUM; POLYBUTENE (1400 MW); PHENYL TRIMETHICONE; LANOLIN ALCOHOLS; CERESIN; MYRISTYL MYRISTATE; HIGH DENSITY POLYETHYLENE; CETYL LACTATE; SHEA BUTTER; CANDELILLA WAX; SILICON DIOXIDE; ZINC; CARNAUBA WAX; ETHYLHEXYL PALMITATE; TRIBEHENIN; SORBITAN ISOSTEARATE; PALMITOYL TRIPEPTIDE-1; PENTAERYTHRITOL TETRAKIS(3-(3,5-DI-TERT-BUTYL-4-HYDROXYPHENYL)PROPIONATE); ISOPROPYL TITANIUM TRIISOSTEARATE; ALUMINUM HYDROXIDE; STEARIC ACID; COPPER; MICA; TITANIUM DIOXIDE; FERRIC OXIDE RED; D&C RED NO. 7

Neutrogena® revitalizing lip balm with sunscreen SPF 20 (All 6 shades*)

Drug Facts

Active ingredients

Octinoxate 7.5%, Oxybenzone 5%

Purpose

Sunscreen

Uses

- helps prevent sunburn

Warnings

- Skin Cancer/Skin Aging Alert: Spending time in the sun increases your risk of skin cancer and early skin aging. This product has been shown only to help prevent sunburn, not skin cancer or early skin aging.
- For external use only

- Do not use on damaged or broken skin

- When using this product keep out of eyes. Rinse with water to remove.

- Stop use and ask a doctor if rash occurs

- Keep out of reach of children. If swallowed, get medical help or contact a Poison Control Center right away.

Directions

For Sunscreen Use

- apply liberally 15 minutes before sun exposure
- use a water resistant sunscreen if swimming or sweating
- reapply at least every 2 hours
- children under 6 months of age: Ask a doctor

Other information

- protect this product from excessive heat and direct sun
- may stain some fabrics

Inactive ingredients

hydrogenated polyisobutene, petrolatum, polybutene, phenyl trimethicone, hydrogenated lanolin, ozokerite, myristyl myristate, polyethylene, cetyl lactate, butyrospermum parkii (shea) butter, bis-behenyl/isostearyl/phytosteryl dimer dilinoleyl dimer dilinoleate, euphorbia cerifera (candelilla) wax, silica, zinc, stearoxymethicone/dimethicone copolymer, copernicia cerifera (carnauba) wax, synthetic wax, ethylhexyl palmitate, tribehenin, sorbitan isostearate, palmitoyl oligopeptide, silica silylate, flavor, pentaerythrityl tetra-di-t-butyl hydroxyhydrocinnamate, isopropyl titanium triisostearate, aluminum hydroxide, stearic acid, copper powder, mica, titanium dioxide, iron oxides, red 7

Questions or comments?

Call toll-free 800-480-4812 or 215-273-8755 (collect) or visit www.neutrogena.com

Distributed by:
JOHNSON & JOHNSON
CONSUMER INC.
Skillman, NJ 08558

PRINCIPAL DISPLAY PANEL - 4.2 g Tube Blister Pack - Fresh Plum 60

FRESH
PLUM 60
SHEER TINT

revitalizing
lip balm
with
sunscreen
SPF 20

Softer, rosier and healthier-looking
lips, even after you take it off!
dramatization

before after

Neutrogena®

NET WT 0.15 OZ (4.2 g)

PRINCIPAL DISPLAY PANEL - 4.2 g Tube Blister Pack - Sheer Shimmer 10

SHEER
SHIMMER 10
SHEER TINT

revitalizing
lip balm
with
sunscreen
SPF 20

Softer, rosier and healthier-looking
lips, even after you take it off!
dramatization

before after

Neutrogena®

NET WT 0.15 OZ (4.2 g)

PRINCIPAL DISPLAY PANEL - 4.2 g Tube Blister Pack - Soft Caramel 50

SOFT
CARAMEL 50
SHEER TINT

revitalizing
lip balm
with
sunscreen
SPF 20

Softer, rosier and healthier-looking
lips, even after you take it off!
dramatization

before after

Neutrogena®

NET WT 0.15 OZ (4.2 g)

PRINCIPAL DISPLAY PANEL - 4.2 g Tube Blister Pack - Healthy Blush 20

HEALTHY
BLUSH 20
SHEER TINT

revitalizing
lip balm
with
sunscreen
SPF 20

Softer, rosier and healthier-looking
lips, even after you take it off!
dramatization

before after

Neutrogena®

NET WT 0.15 OZ (4.2 g)

PRINCIPAL DISPLAY PANEL - 4.2 g Tube Blister Pack - Sunny Berry 30

SUNNY
BERRY 30
SHEER TINT

revitalizing
lip balm
with
sunscreen
SPF 20

Softer, rosier and healthier-looking
lips, even after you take it off!
dramatization

before after

Neutrogena®

NET WT 0.15 OZ (4.2 g)

PRINCIPAL DISPLAY PANEL - 4.2 g Tube Blister Pack - Petal Glow 40

PETAL
GLOW 40
SHEER TINT

revitalizing
lip balm
with
sunscreen
SPF 20

Softer, rosier and healthier-looking
lips, even after you take it off!
dramatization

before after

Neutrogena®

NET WT 0.15 OZ (4.2 g)